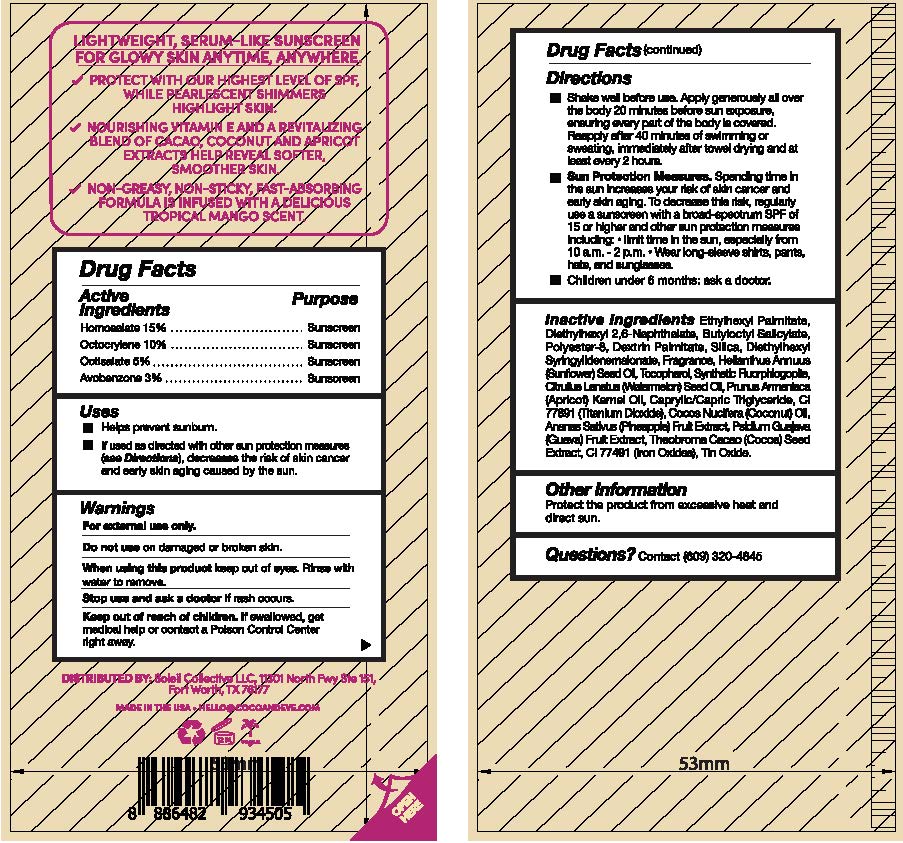 DRUG LABEL: Coco and Eve Sunny Honey Protect SPF 50
NDC: 85624-001 | Form: OIL
Manufacturer: Soleil Collective LLC
Category: otc | Type: HUMAN OTC DRUG LABEL
Date: 20250826

ACTIVE INGREDIENTS: OCTISALATE 5 g/100 g; HOMOSALATE 15 g/100 g; OCTOCRYLENE 10 g/100 g; AVOBENZONE 3 g/100 g
INACTIVE INGREDIENTS: ETHYLHEXYL PALMITATE; PSIDIUM GUAJAVA FRUIT; CAPRYLIC/CAPRIC TRIGLYCERIDE; COCOS NUCIFERA (COCONUT) OIL; DIETHYLHEXYL 2,6-NAPHTHALATE; POLYESTER-8 (1400 MW, CYANODIPHENYLPROPENOYL CAPPED); TOCOPHEROL; APRICOT KERNEL OIL; BUTYLOCTYL SALICYLATE; DEXTRIN PALMITATE (CORN; 20000 MW); SILICA; DIETHYLHEXYL SYRINGYLIDENEMALONATE; HELIANTHUS ANNUUS (SUNFLOWER) SEED OIL; TITANIUM DIOXIDE; CI 77491; CITRULLUS LANATUS (WATERMELON) SEED OIL; MAGNESIUM POTASSIUM ALUMINOSILICATE FLUORIDE; ANANAS SATIVUS (PINEAPPLE) FRUIT; THEOBROMA CACAO (COCOA) SEED POWDER; TIN OXIDE

Highlighter Body SPF 50 (85624-001-15)

Drug Facts

Active ingredients

Homosalate 15%
Octocrylene 10%
Octisalate 5%
Avobenzone 3%

Purpose

Sunscreen

Uses

• Helps prevent sunburn.
• If used as directed with other sun protection measures (see Directions), decreases the risk of skin cancer and early skin aging caused by the sun.

Warnings

For external use only

Do not use

on damaged skin or broken skin

When using this product

keep out of eyes. Rince with water to remove.

Stop use and ask a doctor

if rash occurs

Keep out of reach of children.

If swallowed, get medical help or contact a Poison Control Center right away.

Directions

• Shake well before use. Apply generously all over the body 20 minutes before sun exposure, ensuring every part of the body is covered. Reapply after 40 minutes of swimming or sweating, immediately after towel drying and at least ever 2 hours.
• Sun Protection Measures. Spending time in the sun increases your risk of skin cancer and early skin aging. To decrease this risk, regularly use sunscreen with a broad-spectrum SPF of 15 or higher and other sun protection measures including: • limit time in the sun, especially from 10 a.m. - 2 p.m. • Wear long-sleeved shirts, pants, hats, and sunglasses.
• Children under 6 months: ask a doctor.

Other information

Protect the product from excessive heat and direct sun.

Inactive ingredients

ETHYLHEXYL PALMITATE, DIETHYLHEXYL 2,6-NAPHTHALATE, BUTYLOCTYL SALICYLATE, POLYESTER-8, DEXTRIN PALMITATE, SILICA, DIETHYLHEXYL SYRINGYLIDENEMALONATE, PARFUM (FRAGRANCE), HELIANTHUS ANNUUS (SUNFLOWER) SEED OIL, TOCOPHEROL, SYNTHETIC FLUORPHLOGOPITE, CITRULLUS LANATUS (WATERMELON) SEED OIL, PRUNUS ARMENIACA (APRICOT) KERNEL OIL, CAPRYLIC/CAPRIC TRIGLYCERIDE, CI 77891 (TITANIUM DIOXIDE), COCOS NUCIFERA (COCONUT) OIL, ANANAS SATIVUS (PINEAPPLE) FRUIT EXTRACT, PSIDIUM GUAJAVA FRUIT EXTRACT, THEOBROMA CACAO (COCOA) SEED EXTRACT, CI 77491 (IRON OXIDES), TIN OXIDE.

Questions?

Contact (609) 320-4845